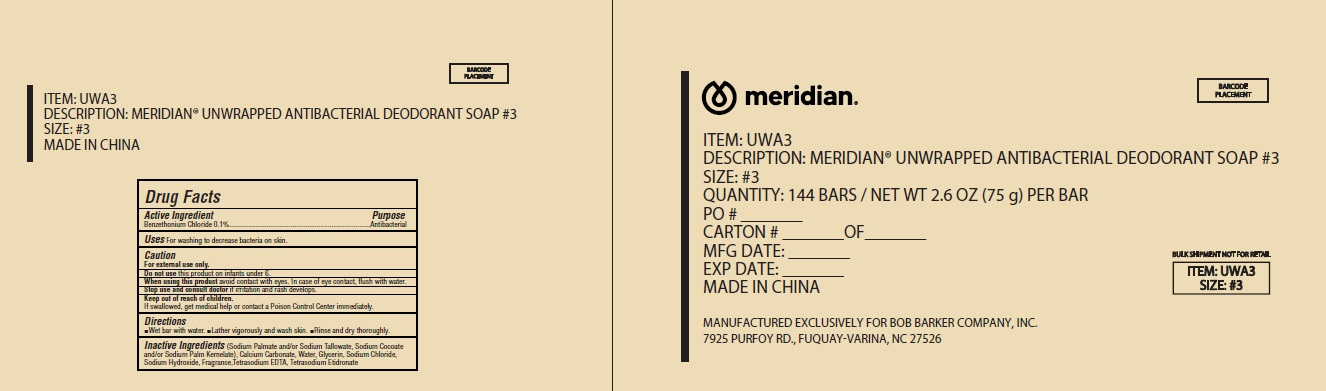 DRUG LABEL: Meridian Unwrapped Antibacterial Deodorant
NDC: 71035-003 | Form: SOAP
Manufacturer: Yangzhou Hongshengding Chemical Co.,Ltd.
Category: otc | Type: HUMAN OTC DRUG LABEL
Date: 20250728

ACTIVE INGREDIENTS: BENZETHONIUM CHLORIDE 0.1 g/100 g
INACTIVE INGREDIENTS: SODIUM PALMATE; WATER; SODIUM PALM KERNELATE; CALCIUM CARBONATE; SODIUM CHLORIDE; GLYCERIN; SODIUM HYDROXIDE; EDETATE SODIUM; TETRASODIUM ETIDRONATE; SODIUM TALLOWATE; SODIUM COCOATE

71035_003 Meridian Unwraped Antibacterial deodorant Soap

Active Ingredient

Benzethonium Chloride 0.1%

Purpose

Antibacterial

Use

For washing to decrease bacteria on skin

Warnings

For external use only

Do not use this product on infants under 6

When using this product avoid contact with eyes. In case of eye contact flush with water

Stop use and consult a doctor if irritation and rash develop

Keep out of reach of children. If swallowed, get medical help or contact a Poison Control Center immediately

Directions

Wet bar with water

Lather vigorously and wash skin

Rinse and dry thoroughly

Inactive ingredients

Soap (Sodium Palmate and/or Sodium Tallowate, Sodium Cocoate and/or Sodium Palm Kernelate), Calcium Carbonate, Water, Glycerin, Sodium Hydroxide, Fragrance, Tetrasodium EDTA, Tetrasodium Etidronate